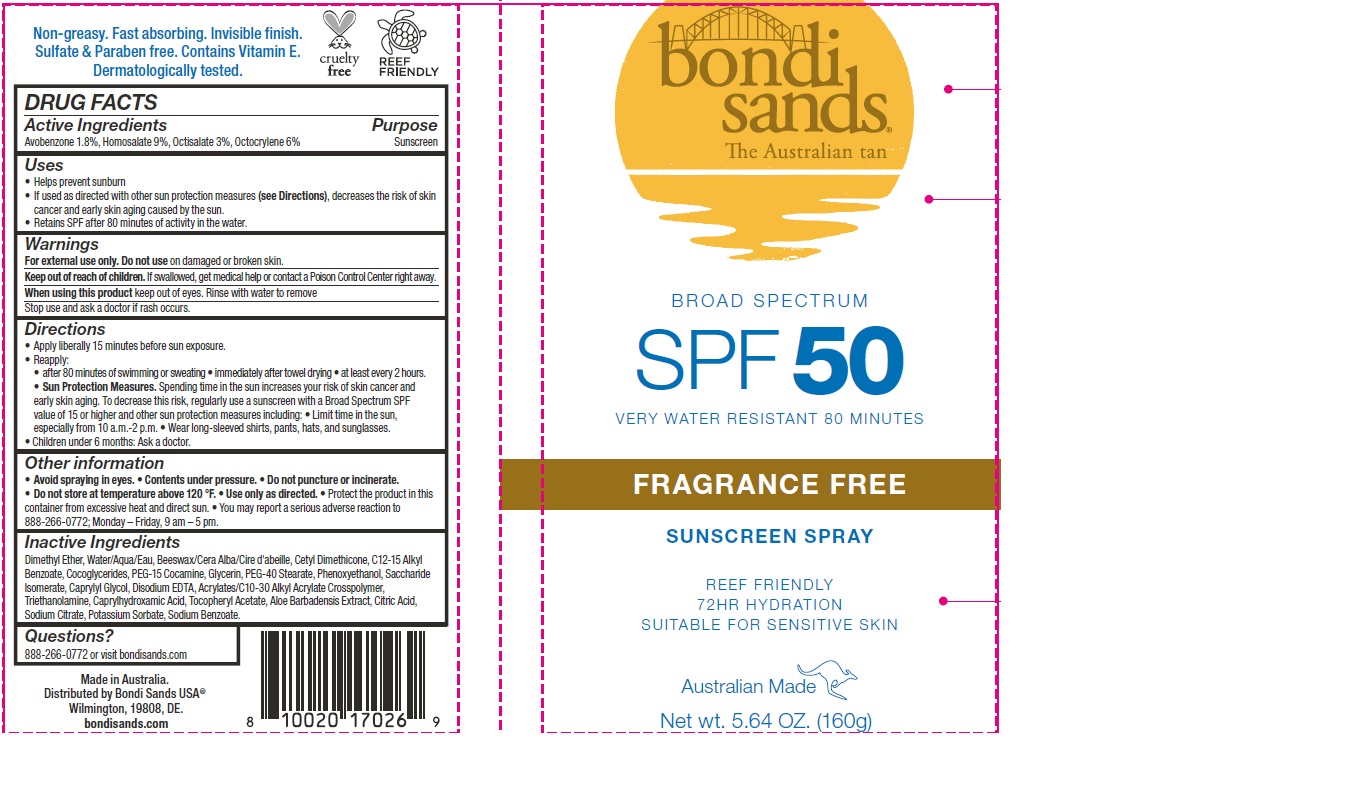 DRUG LABEL: Bondi Sands Fragrance Free SPF 50 Sunscreen
NDC: 79950-003 | Form: AEROSOL, SPRAY
Manufacturer: BONDI SANDS (USA) INC.
Category: otc | Type: HUMAN OTC DRUG LABEL
Date: 20241106

ACTIVE INGREDIENTS: AVOBENZONE 18 mg/1 g; OCTISALATE 30 mg/1 g; OCTOCRYLENE 60 mg/1 g; HOMOSALATE 90 mg/1 g
INACTIVE INGREDIENTS: POTASSIUM SORBATE; SODIUM BENZOATE; DIMETHYL ETHER; SODIUM CITRATE; YELLOW WAX; PEG-15 COCAMINE; PHENOXYETHANOL; SACCHARIDE ISOMERATE; CAPRYLYL GLYCOL; COCO-GLYCERIDES; .ALPHA.-TOCOPHEROL ACETATE; GLYCERIN; EDETATE DISODIUM; TROLAMINE; CAPRYLHYDROXAMIC ACID; ALOE VERA WHOLE; CITRIC ACID MONOHYDRATE; PEG-40 STEARATE; WATER; ALKYL (C12-15) BENZOATE; CETYL DIMETHICONE 45; CARBOMER COPOLYMER TYPE B (ALLYL PENTAERYTHRITOL CROSSLINKED)

Bondi Sands Fragrance Free SPF 50 Sunscreen

Active Ingredients

Avobenzone 1.8%, Homosalate 9%, Octisalate 3%, Octocrylene 6%

Purpose

Sunscreen

Uses

- Helps prevent sunburn
- If used as directed with other sun protection measures (see Directions), decreases the risk of skin cancer and early skin aging caused by the sun.
- Retains SPF after 80 minutes of activity in the water.

Warnings

For external use only.

Do not use

on damaged or broken skin.

Keep out of reach of children.

If swallowed, get medical help or contact a Poison Control Center right away.

When using this product

keep out of eyes. Rinse with water to remove

Stop use and ask a doctor

if rash occurs

Directions

- Apply liberally 15 minutes before sun exposure.
- Reapply:
- after 80 minutes of swimming or sweating
- immediately after towel drying
- at least every 2 hours.
- Sun Protection Measures. Spending time in the sun increases your risk of skin cancer and early skin aging. To decrease this risk, regularly use a sunscreen with a Broad Spectrum SPF value of 15 or higher and other sun protection measures including:
- Limit time in the sun, especially from 10 a.m.- 2 p.m.
- Wear long sleeved shirts, pants, hats, and sunglasses.
- Children under 6 months: Ask a doctor.

Other information

- Avoid spraying in eyes.
- Contents under pressure.
- Do not puncture or incinerate.
- Do not store at temperature above 120 °F.
- Use only as directed.
- Protect the product in this container from excessive heat and direct sun.
- You may report a serious adverse reaction to 888-266-0772; Monday – Friday, 9 am – 5 pm.

Inactive Ingredients

Dimethyl Ether, Water/Aqua/Eau, Beeswax/Cera Alba/Cire d'abeille, Cetyl Dimethicone, C12-15 Alkyl Benzoate, Cocoglycerides, PEG-15 Cocamine, Glycerin, PEG-40 Stearate, Phenoxyethanol, Saccharide Isomerate, Caprylyl Glycol, Disodium EDTA, Acrylates/C10-30 Alkyl Acrylate Crosspolymer, Triethanolamine, Caprylhydroxamic Acid, Tocopheryl Acetate, Aloe Barbadensis Extract, Citric Acid, Sodium Citrate, Potassium Sorbate, Sodium Benzoate.

Questions?

888-266-0772 or visit bondisands.com

Company Information

Made in Australia.

Distributed by Bondi Sands USA

Wilmingon, 19808, DE.

bondisands.com

Product Packaging

bondi sands

The Australian tan

BROAD SPECTRUM

SPF 50

VERY WATER RESISTANT 80 MINUTES

FRAGRANCE FREE

SUNSCREEN SPRAY

REEF FRIENDLY

72HR HYDRATION

SUITABLE FOR SENSITIVE SKIN

Australian Made

Net wt. 5.64 OZ. (160g)